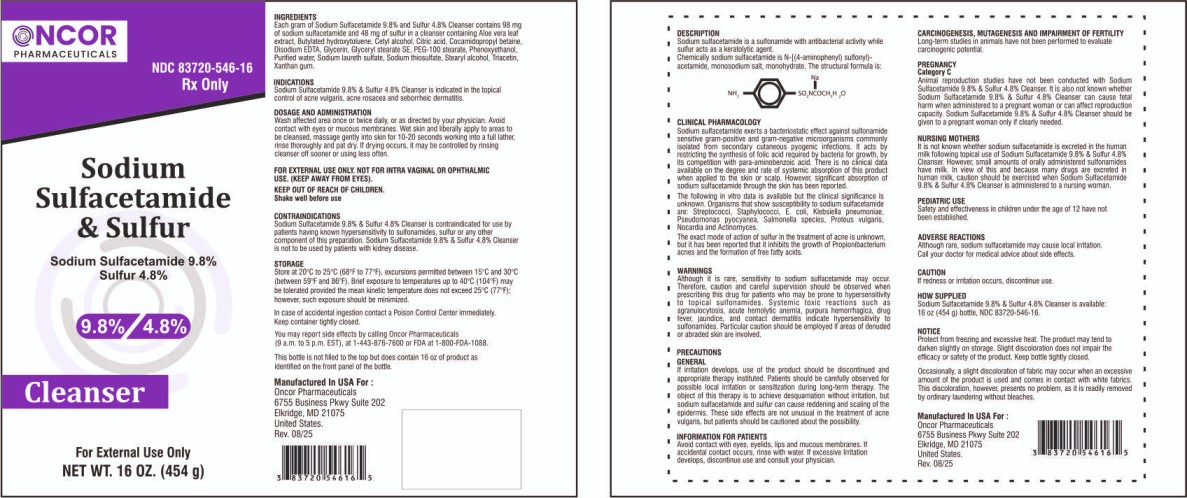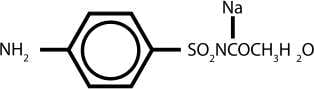 DRUG LABEL: Sodium Sulfacetamide 9.8% Sulfur 4.8% Cleanser
NDC: 83720-546 | Form: LIQUID
Manufacturer: Oncor Pharmaceuticals
Category: prescription | Type: HUMAN PRESCRIPTION DRUG LABEL
Date: 20260211

ACTIVE INGREDIENTS: SULFACETAMIDE SODIUM 98 mg/1 g; SULFUR 48 mg/1 g
INACTIVE INGREDIENTS: ALOE VERA LEAF; BUTYLATED HYDROXYTOLUENE; CETYL ALCOHOL; CITRIC ACID; COCAMIDOPROPYL BETAINE; EDETATE DISODIUM; GLYCERIN; GLYCERYL STEARATE SE; PEG-100 STEARATE; PHENOXYETHANOL; WATER; SODIUM LAURETH SULFATE; SODIUM THIOSULFATE; STEARYL ALCOHOL; TRIACETIN; XANTHAN GUM

Sodium Sulfacetamide 9.8% Sulfur 4.8% Cleanser

DESCRIPTION

Sodium sulfacetamide is a sulfonamide with antibacterial activity while sulfur acts as a keratolytic agent.

Chemically sodium sulfacetamide is N-[(4-aminophenyl) sulfonyl)-acetamide, monosodium salt, monohydrate. The structural formula is:

Each gram of Sodium Sulfacetamide 9.8% and Sulfur 4.8% Cleanser contains 98 mg of sodium sulfacetamide and 48 mg of sulfur in a cleanser containing Aloe vera leaf extract, Butylated hydroxytoluene, Cetyl alcohol, Citric acid, Cocamidopropyl betaine, Disodium EDTA, Glycerin, Glyceryl stearate SE, PEG-100 stearate, Phenoxyethanol, Purified water, Sodium laureth sulfate, Sodium thiosulfate, Stearyl alcohol, Triacetin, Xanthan gum.

INDICATIONS

Sodium Sulfacetamide 9.8% & Sulfur 4.8% Cleanser is indicated in the topical control of acne vulgaris, acne rosacea and seborrheic dermatitis.

DOSAGE AND ADMINISTRATION

Wash affected area once or twice daily, or as directed by your physician. Avoid contact with eyes or mucous membranes. Wet skin and liberally apply to areas to be cleansed, massage gently into skin for 10-20 seconds working into a full lather, rinse thoroughly and pat dry. If drying occurs, it may be controlled by rinsing cleanser off sooner or using less often.

INSTRUCTIONS FOR USE

FOR EXTERNAL USE ONLY. NOT FOR INTRA VAGINAL OR OPHTHALMIC USE. (KEEP AWAY FROM EYES).
KEEP OUT OF REACH OF CHILDREN.
Shake well before use

CONTRAINDICATIONS

Sodium Sulfacetamide 9.8% & Sulfur 4.8% Cleanser is contraindicated for use by patients having known hypersensitivity to sulfonamides, sulfur or any other component of this preparation. Sodium Sulfacetamide 9.8% & Sulfur 4.8% Cleanser is not to be used by patients with kidney disease.

CAUTION

If redness or irritation occurs, discontinue use.

STORAGE

Store at 20°C to 25°C (68°F to 77°F), excursions permitted between 15°C and 30°C (between 59°F and 86°F). Brief exposure to temperatures up to 40°C (104°F) may be tolerated provided the mean kinetic temperature does not exceed 25°C (77°F); however, such exposure should be minimized.

OTHER SAFETY INFORMATION

In case of accidental ingestion contact a Poison Control Center immediately. Keep container tightly closed.

You may report side effects by ca ling Oncor Pharmaceuticals (9 a.m. to 5 p.m. EST), at 1-443-876-7600 or FDA at 1-800-FDA-1088.

CLINICAL PHARMACOLOGY

Sodium sulfacetamide exerts a bacteriostatic effect against sulfonamide sensitive gram-positive and gram-negative microorganisms commonly isolated from secondary cutaneous pyogenic infections. It acts by restricting the synthesis of folic acid required by bacteria for growth, by its competition with para-aminobenzoic acid. There is no clinical data available on the degree and rate of systemic absorption of this product when applied to the skin or scalp. However, significant absorption of sodium sulfacetamide through the skin has been reported.

The following in vitro data is available but the clinical significance is unknown. Organisms that show susceptibility to sodium sulfacetamide are: Streptococci, Staphylococci, E. coli, Klebsiella pneumoniae, Pseudomonas pyocyanea, Salmone la species, Proteus vulgaris, Nocardia and Actinomyces.

The exact mode of action of sulfur in the treatment of acne is unknown, but it has been reported that it inhibits the growth of Propionibacterium acnes and the formation of free fatty acids.

WARNINGS

Although it is rare, sensitivity to sodium sulfacetamide may occur. Therefore, caution and careful supervision should be observed when prescribing this drug for patients who may be prone to hypersensitivity to topical sulfonamides. Systemic toxic reactions such as agranulocytosis, acute hemolytic anemia, purpura hemorrhagica, drug fever, jaundice, and contact dermatitis indicate hypersensitivity to sulfonamides. Particular caution should be employed if areas of denuded or abraded skin are involved.

PRECAUTIONS GENERAL

If irritation develops, use of the product should be discontinued and appropriate therapy instituted. Patients should be carefully observed for possible local irritation or sensitization during long-term therapy. The object of this therapy is to achieve desquamation without irritation, but sodium sulfacetamide and sulfur can cause reddening and scaling of the epidermis. These side effects are not unusual in the treatment of acne vulgaris, but patients should be cautioned about the possibility.

INFORMATION FOR PATIENTS

Avoid contact with eyes, eyelids, lips and mucous membranes. If accidental contact occurs, rinse with water. If excessive Irritation develops, discontinue use and consult your physician.

CARCINOGENESIS, MUTAGENESIS AND IMPAIRMENT OF FERTILITY

Long-term studies in animals have not been performed to evaluate carcinogenic potential.

PREGNANCY Category C

Animal reproduction studies have not been conducted with Sodium Sulfacetamide 9.8% & Sulfur 4.8% Cleanser. It is also not known whether Sodium Sulfacetamide 9.8% & Sulfur 4.8% Cleanser can cause fetal harm when administered to a pregnant woman or can affect reproduction capacity. Sodium Sulfacetamide 9.8% & Sulfur 4.8% Cleanser should be given to a pregnant woman only if clearly needed.

NURSING MOTHERS

It is not known whether sodium sulfacetamide is excreted in the human milk following topical use of Sodium Sulfacetamide 9.8% & Sulfur 4.8% Cleanser. However, small amounts of orally administered sulfonamides have milk. In view of this and because many drugs are excreted in human milk, caution should be exercised when Sodium Sulfacetamide 9.8% & Sulfur 4.8% Cleanser is administered to a nursing woman.

PEDIATRIC USE

Safety and effectiveness in children under the age of 12 have not been established.

ADVERSE REACTIONS

Although rare, sodium sulfacetamide may cause local irritation. Call your doctor for medical advice about side effects.

HOW SUPPLIED

Sodium Sulfacetamide 9.8% & Sulfur 4.8% Cleanser is available:
16 oz (454 g) bottle, NDC 83720-546-16.

NOTICE

Protect from freezing and excessive heat. The product may tend to darken slightly on storage. Slight discoloration does not impair the efficacy or safety of the product. Keep bottle tightly closed.

Occasionally, a slight discoloration of fabric may occur when an excessive amount of the product is used and comes in contact with white fabrics. This discoloration, however, presents no problem, as it is readily removed by ordinary laundering without bleaches.

PACKAGE LABEL

Manufactured In USA For :
Oncor Pharmaceuticals
6755 Business Pkwy Suite 202
Elkridge, MD 21075
United States.
Rev. 08/25